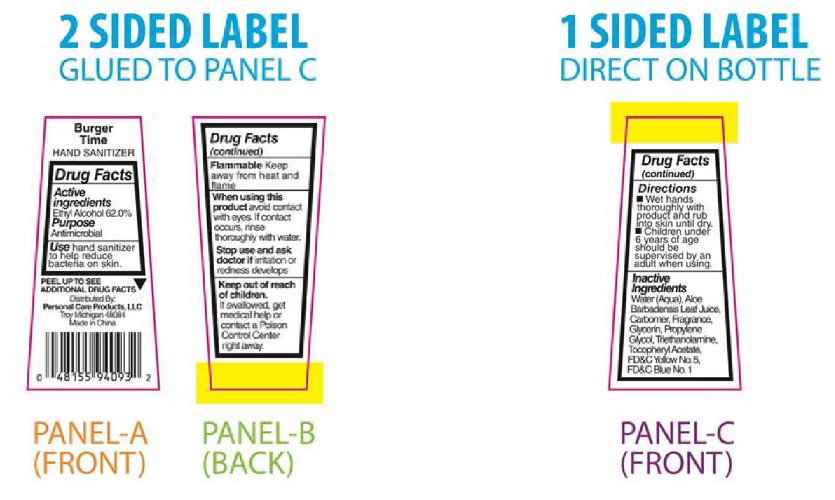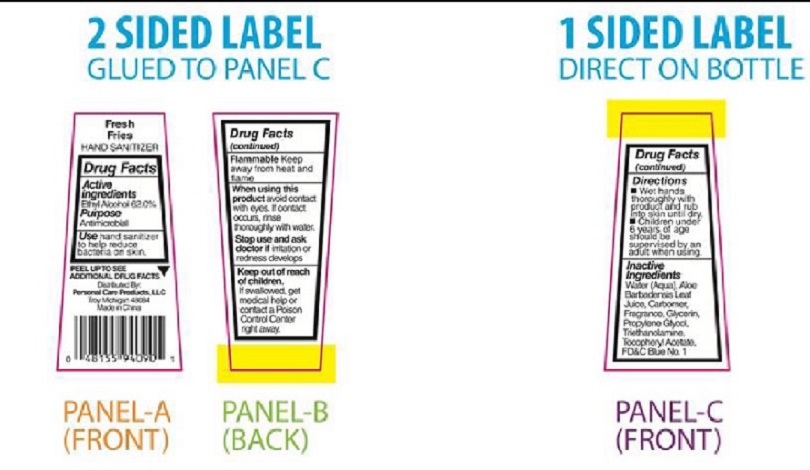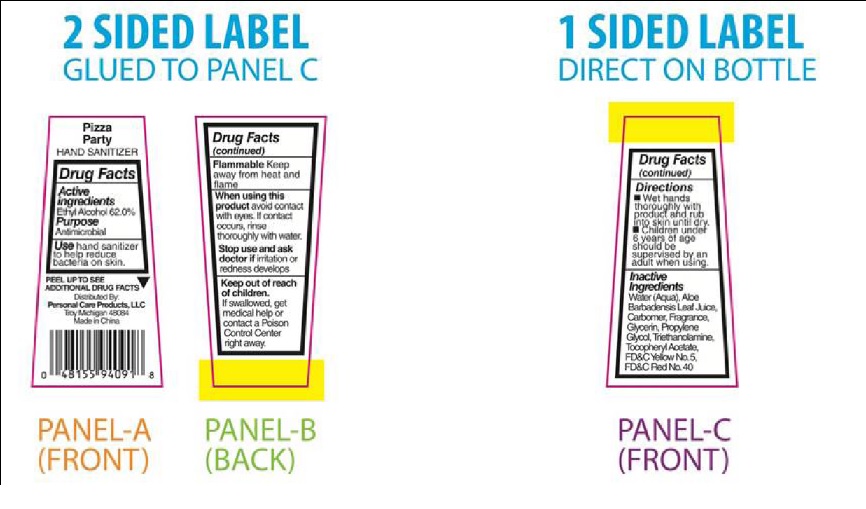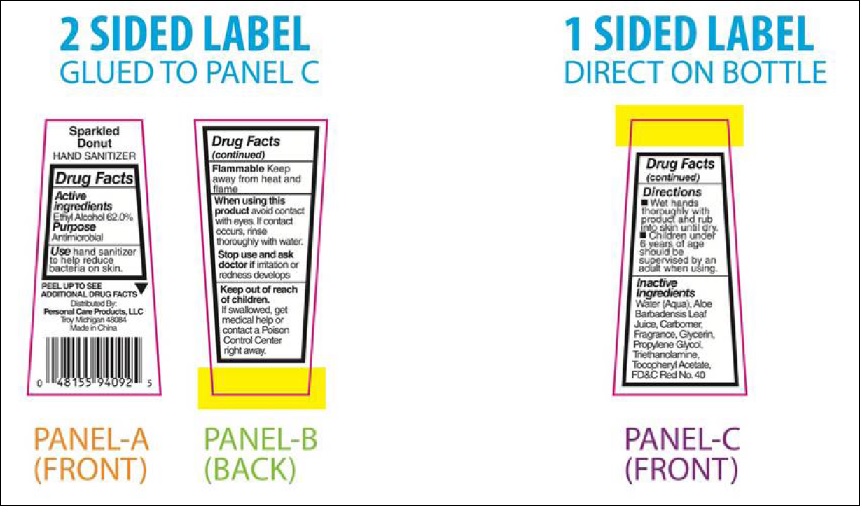 DRUG LABEL: Burger Time
NDC: 29500-9413 | Form: LIQUID
Manufacturer: GL 360
Category: otc | Type: HUMAN OTC DRUG LABEL
Date: 20180424

ACTIVE INGREDIENTS: ALCOHOL 17.57 g/30 mL
INACTIVE INGREDIENTS: WATER; ALOE VERA LEAF; CARBOXYPOLYMETHYLENE; GLYCERIN; PROPYLENE GLYCOL; TROLAMINE; .ALPHA.-TOCOPHEROL ACETATE; FD&C YELLOW NO. 5; FD&C BLUE NO. 1

Burger Time -9413
Fresh Fries -9414
Pizza Party -9415
Sparkled Donut -9516

Drug Facts

Active Ingredients

Ethyl Alcohol 62%

Purpose

Antimicrobial

INDICATIONS AND USAGE

Use hand sanitizer to help reduce bacteria on skin.

Warning

Flammable Keep away from heat and flame

When using this product avoid contact with eyes. If contact occurs, rinse thoroughly with water.

Stop use and ask doctor if irritation or redness develops

Keep out of reach of children. If swallowed, get medical help or contact a Poison Control Center right away.

Directions

■ Wet hands thoroughly with product and rub into skin until dry.
■ Children Directions
■ Wet hands thoroughly with product and rub into skin until dry.
■ Children under 6 years of age should be supervised by an
adult when using.

Inactive
Ingredients
Water (Aqua), Aloe Barbadensis Leaf Juice, Carbomer, Fragrance,
Glycerin, Propylene Glycol, Triethanolamine, Tocopheryl Acetate
FD&C Yellow No. 5, FD&C Blue No. 1

Product Labels for: Burger Time Fresh Fries Pizza Party Sparkled Donut

Burger Time Hand Sanitizer Label

Burger Time

HAND SANITIZER

Drug Facts

Active
Ingredients
Ethyl Alcohol 62.0%

Purpose
Antimicrobial

Use hand sanitizer
to help reduce
bacteria on skin.

ADDITIONAL DRUG FACTS

Distributed By:
Personal Care Products, LLC
Troy, Michigan 48084
Made in China

Drug Facts
(continued)

Flammable Keep
away from heat and
flame

When using this
product avoid contact
with eyes. If contact
occurs, rinse
thoroughly with water.

Stop use and ask
doctor if irritation or
redness develops

Keep out of reach
of children.
If swallowed, get
medical help or
contact a Poison
Control Center
right away.

Drug Facts
(continued)

Directions
■ Wet hands
thoroughly with
product and rub
into skin until dry.
■ Children under
6 years of age
should be
supervised by an
adult when using.

Inactive
Ingredients
Water (Aqua), Aloe
Barbadensis Leaf Juice,
Carbomer, Fragrance,
Glycerin, Propylene
Glycol, Triethanolamine,
Tocopheryl Acetate
FD&C Yellow No. 5,
FD&C Blue No. 1

Fresh Fries Hand Sanitizer Label

Pizza Party Hand Sanitizer Label

Sparkled Donut Hand Sanitizer Label